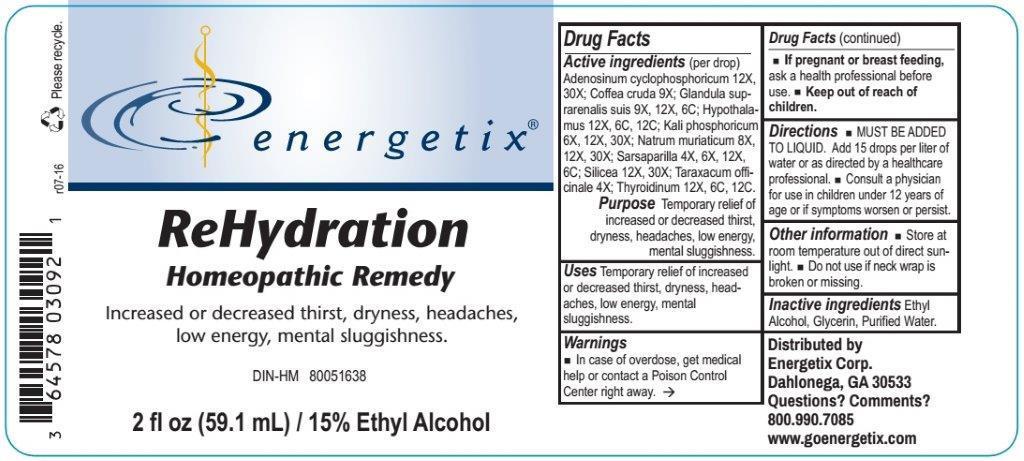 DRUG LABEL: Rehydration
NDC: 64578-0116 | Form: LIQUID
Manufacturer: Energetix Corp
Category: homeopathic | Type: HUMAN OTC DRUG LABEL
Date: 20170103

ACTIVE INGREDIENTS: ADENOSINE CYCLIC PHOSPHATE 12 [hp_X]/1 mL; ARABICA COFFEE BEAN 9 [hp_X]/1 mL; SUS SCROFA ADRENAL GLAND 9 [hp_X]/1 mL; BOS TAURUS HYPOTHALAMUS 12 [hp_X]/1 mL; POTASSIUM PHOSPHATE, DIBASIC 6 [hp_X]/1 mL; SODIUM CHLORIDE 8 [hp_X]/1 mL; SMILAX REGELII ROOT 4 [hp_X]/1 mL; SILICON DIOXIDE 12 [hp_X]/1 mL; TARAXACUM OFFICINALE 4 [hp_X]/1 mL; THYROID, BOVINE 12 [hp_X]/1 mL
INACTIVE INGREDIENTS: WATER; GLYCERIN; ALCOHOL

Drug Facts:

Active ingredients (per drop)

Adenosinum cyclophosphoricum 12X, 30X, Coffea cruda 9X, Glandula suprarenalis suis 9X, 12X, 6C, Hypothalamus 12X, 6C, 12C, Kali phosphoricum 6X, 12X, 30X, Natrum muriaticum 8X, 12X, 30X, Sarsaparilla 4X, 6X, 12X, 6C, Silicea 12X, 30X, Taraxacum officinale 4X, Thyroidinum 12X, 6C, 12C.

Purpose

Temporary relief of increased or decreased thirst, dryness, headaches, low energy, mental sluggishness.

Uses

Temporary relief of increased or decreased thirst, dryness, headaches, low energy, mental sluggishness.

Warnings

- In case of overdose, get medical help or contact a Poison Control Center right away.
- If pregnant or breast feeding, ask a health professional before use.
- Keep out of reach of children.

Keep out of reach of children.

Directions

- MUST BE ADDED TO LIQUID. Add 15 drops per liter of water or as directed by a healthcare professional.
- Consult a physician for use in children under 12 years of age or if symptoms worsen or persist.

Other information

- Store at room temperature out of direct sunlight.
- Do not use if neck wrap is broken or missing.

Inactive ingredients

Ethyl Alcohol, Glycerin, Purified Water.

QUESTIONS

Distributed by

Energetix Corp.

Dahlonega, GA 30533

Questions? Comments?

800.990.7085

www.goenergetix.com

PURPOSE

Increased or decreased thirst, dryness, headaches, low energy, mental sluggishness.

PACKAGE LABEL

energetix

ReHydration

Homeopathic Remedy

Increased or decreased thirst, dryness, headaches, low energy, mental sluggishness.

DIN-HM 80051638

2 fl oz (59.1 mL) / 15% Ethyl Alcohol